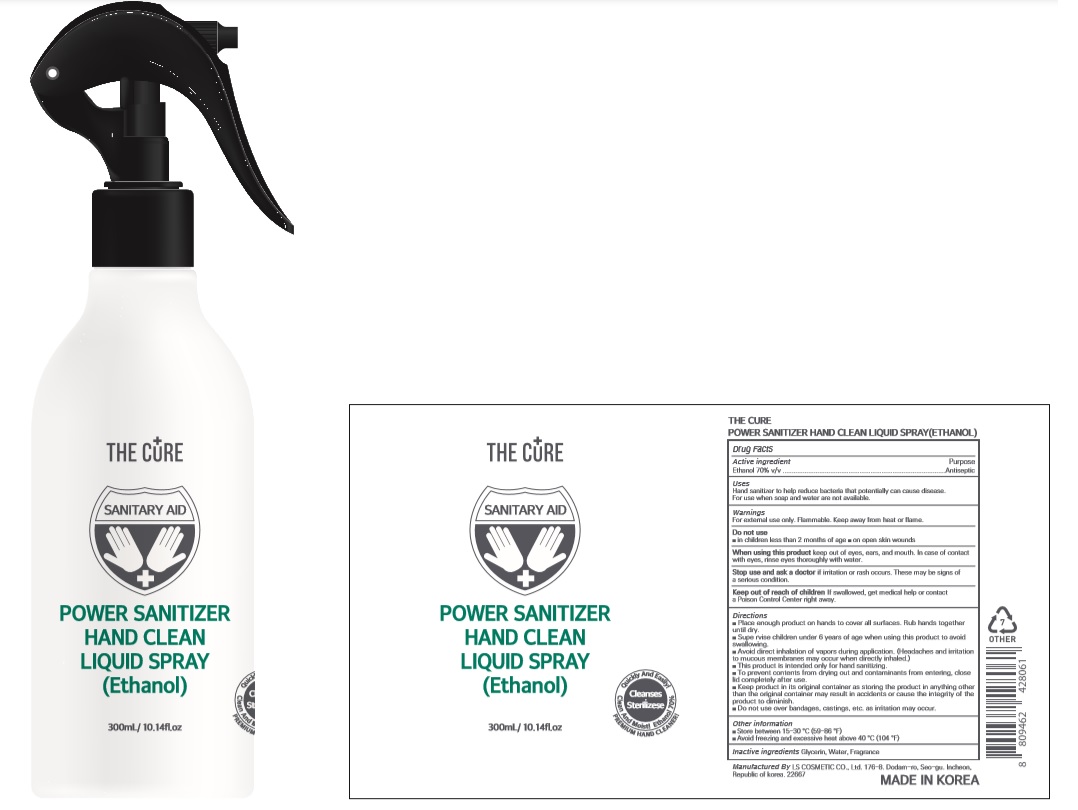 DRUG LABEL: THE CURE POWER SANITIZER HAND CLEAN LIQUIDSpray(Ethanol)
NDC: 59545-1370 | Form: SPRAY
Manufacturer: LS COSMETIC CO.,LTD.
Category: otc | Type: HUMAN OTC DRUG LABEL
Date: 20200615

ACTIVE INGREDIENTS: ALCOHOL 210 mL/300 mL
INACTIVE INGREDIENTS: GLYCERIN; WATER

THE CURE POWER SANITIZER HAND CLEAN LIQUID SPRAY(Ethanol) : 59545-1370-1 | 300 mL | Bottle+Spray